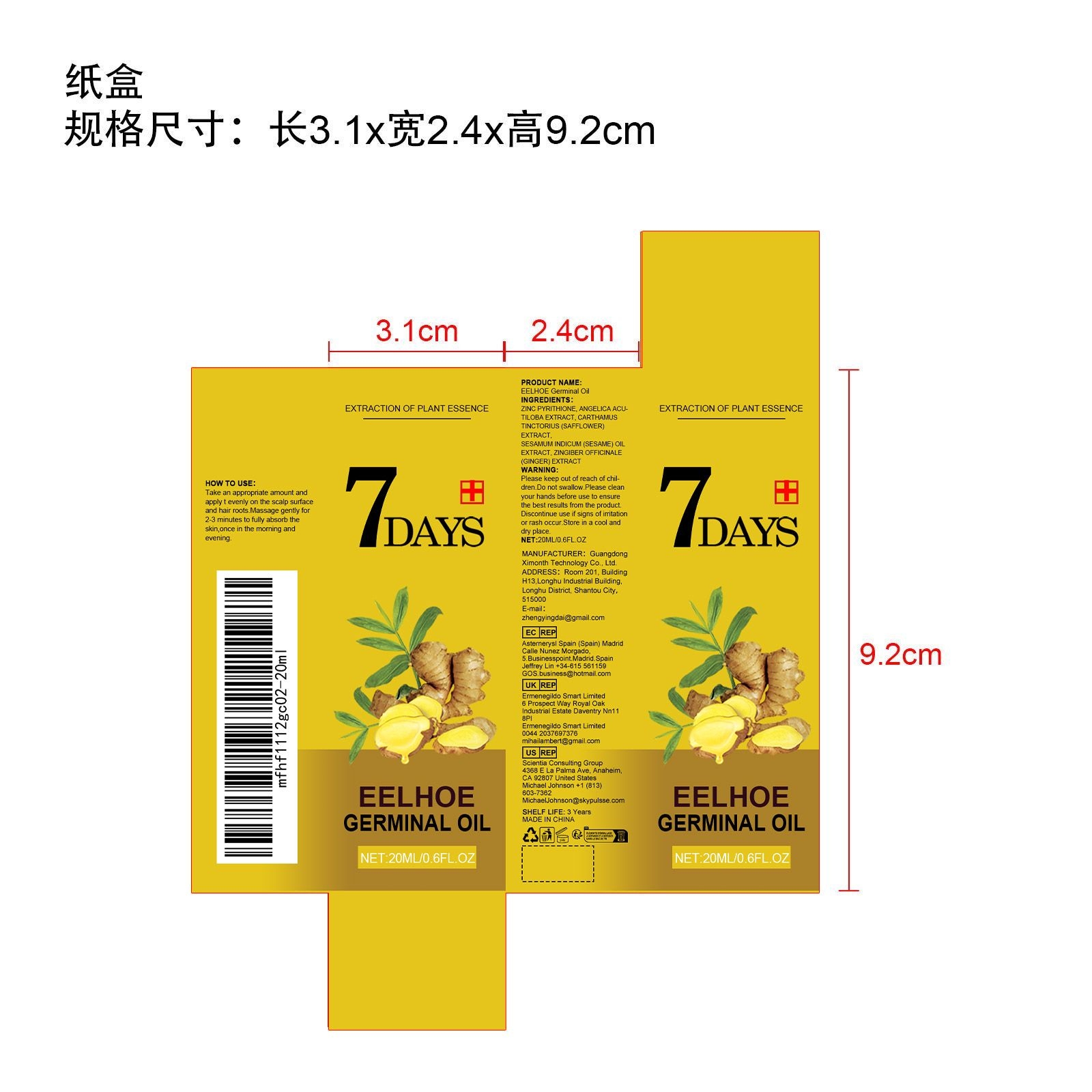 DRUG LABEL: Germinal Oil
NDC: 84660-017 | Form: OIL
Manufacturer: Guangdong Ximonth Technology Co., Ltd.
Category: otc | Type: HUMAN OTC DRUG LABEL
Date: 20240921

ACTIVE INGREDIENTS: SAFFLOWER 4 mg/20 mg; SESAME OIL UNSAPONIFIABLES 3 mg/20 mg; GINGER OIL 2 mg/20 mg; ANGELICA ACUTILOBA WHOLE 5 mg/20 mg
INACTIVE INGREDIENTS: PYRITHIONE ZINC 6 mg/20 mg

Active Ingredient(s)

ANGELICA ACUTILOBA EXTRACT、CARTHAMUS TINCTORIUS (SAFFLOWER) EXTRACT、SESAMUM INDICUM (SESAME) OIL EXTRACT、ZINGIBER OFFICINALE (GINGER) EXTRACT

Purpose

Strengthen hair roots, reduce hair breakage and shedding, improve hair toughness, and make hair strong and thick

Use

Take an appropriate amount and apply t evenly on the scalp surface and hair roots.Massage gently for 2-3 minutes to fully absorb the skin,once in the morning and evening.

Warnings

Please keep out of reach of children.Do not swallow.Please clean your hands before use to ensure the best results from the product.Discontinue use if signs of irritation or rash occur.Store in a cool and dry place.

Do not use

Discontinue use if signs of irritation or rash occur.

STOP USE

Discontinue use if signs of irritation or rash occur.

KEEP OUT OF REACH OF CHILDREN

Please keep out of reach of children. Do not swallow.

STORAGE AND HANDLING

Avoid freezing and excessive heat above 40C (104F) ）

Store in a cool and dry place.

INACTIVE INGREDIENT

ZINC PYRITHIONE